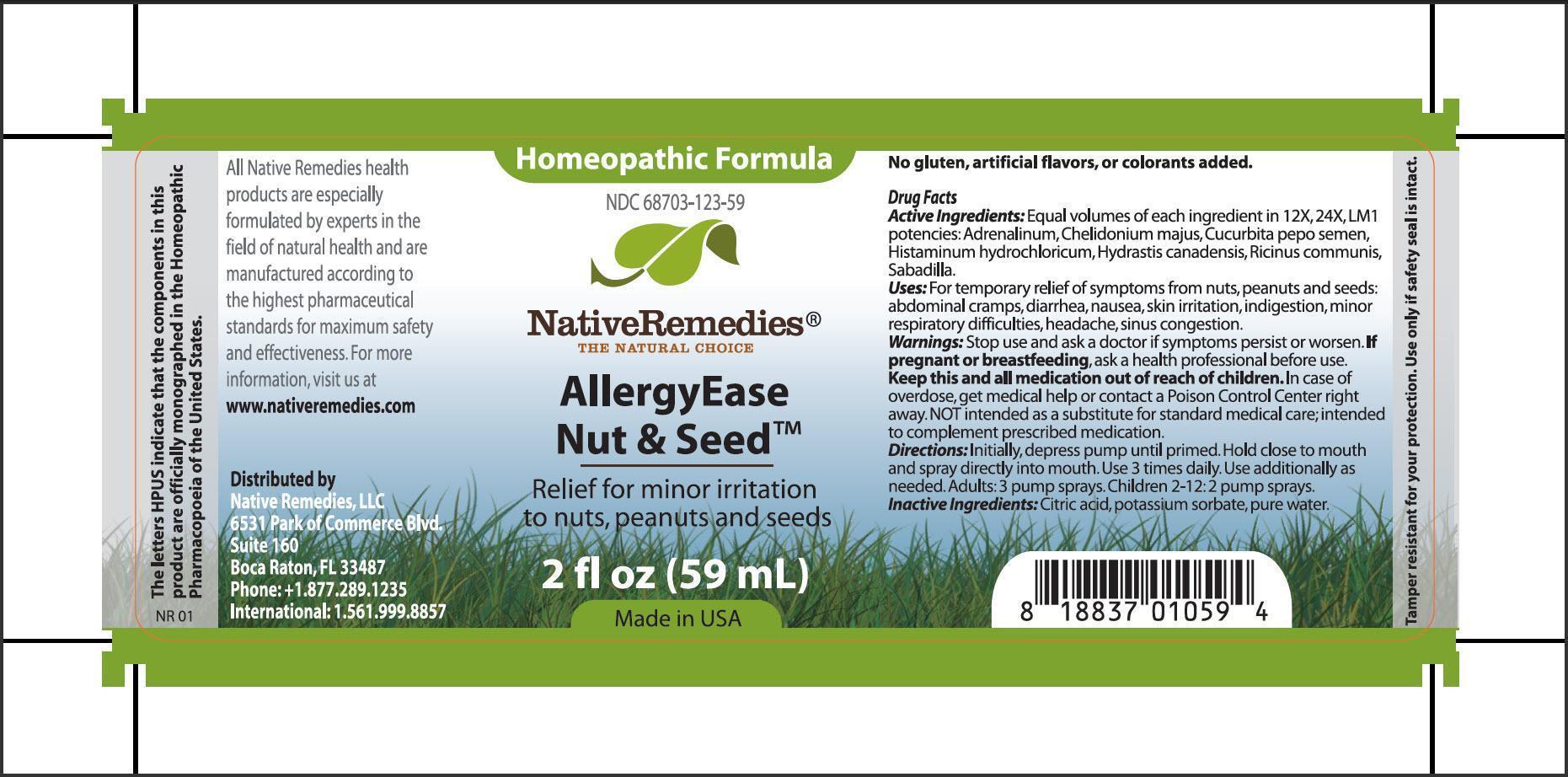 DRUG LABEL: AllergyEase Nut and Seed
NDC: 68703-123 | Form: SPRAY
Manufacturer: Native Remedies, LLC
Category: homeopathic | Type: HUMAN OTC DRUG LABEL
Date: 20130729

ACTIVE INGREDIENTS: EPINEPHRINE 12 [hp_X]/59 mL; CHELIDONIUM MAJUS 12 [hp_X]/59 mL; PUMPKIN SEED  12 [hp_X]/59 mL; HISTAMINE DIHYDROCHLORIDE 12 [hp_X]/59 mL; GOLDENSEAL 12 [hp_X]/59 mL; RICINUS COMMUNIS SEED 12 [hp_X]/59 mL; SCHOENOCAULON OFFICINALE SEED 12 [hp_X]/59 mL
INACTIVE INGREDIENTS: CITRIC ACID MONOHYDRATE; POTASSIUM SORBATE; WATER

AllergyEase Nut and Seed

PURPOSE

Relief for minor irritation to nuts, peanuts and seeds

Drug Facts
Active Ingredients:Equal volumes of each ingredient in 12X, 24X, LM1 potencies: Adrenalinum, Chelidonium majus, Cucurbita pepo semen, Hsitaminum hydrochloricum, Hydrastis canadensis, Ricinus communis, sabadilla

INDICATIONS AND USAGE

Uses: For temporary relief of symptoms from nuts, peanuts and seeds: abdominal cramps, diarrhea, nausea, skin irritation, indigestion, minor respiratory difficulties, headache, sinus congestion

WARNINGS

Warnings: Stop use and ask a doctor if symptoms persist or worsen

PREGNANCY OR BREAST FEEDING

If pregnant or breastfeeding, ask a health professional before use

KEEP OUT OF REACH OF CHILDREN

Keep this and all medication out of reach of children

OVERDOSAGE

In case of overdose, get medical help or contact a Poison Control Center right away. NOT intended as a substitute for standard medical care, intended to complement prescribed medication

DOSAGE AND ADMINISTRATION

Directions: Initially, depress pump until primed. Hold close to mouth and spray directly into mouth,. Use 3 times daily. Use additionally as needed. Adults: 3 pumps sprays. Children 2-12: 2 pump sprays

Inactive Ingredients: Citric acid, potassium sorbate, pure water

PATIENT COUNSELING INFORMATION

The letters HPUS indicate that the components in this product are officially monographed in the Homeopathic Pharmacopoeia of the United States

All Native Remedies health products are especially formulated by experts in the field of natural health and are manufactured according to the highest pharmaceutical standards for maximum safety and effectiveness. For more information, visit us at www.nativeremedies.com

Distributed by
Native Remedies, LLC
6531 Park of Commerce Blvd.
Suite 160
Boca Raton, FL 33487
Phone: +1.877.289.1235
International: 1.561.999.8857

No gluten, artificial flavors, or colorants added

STORAGE AND HANDLING

Tamper resistant for your protection. Use only if safety seal is intact